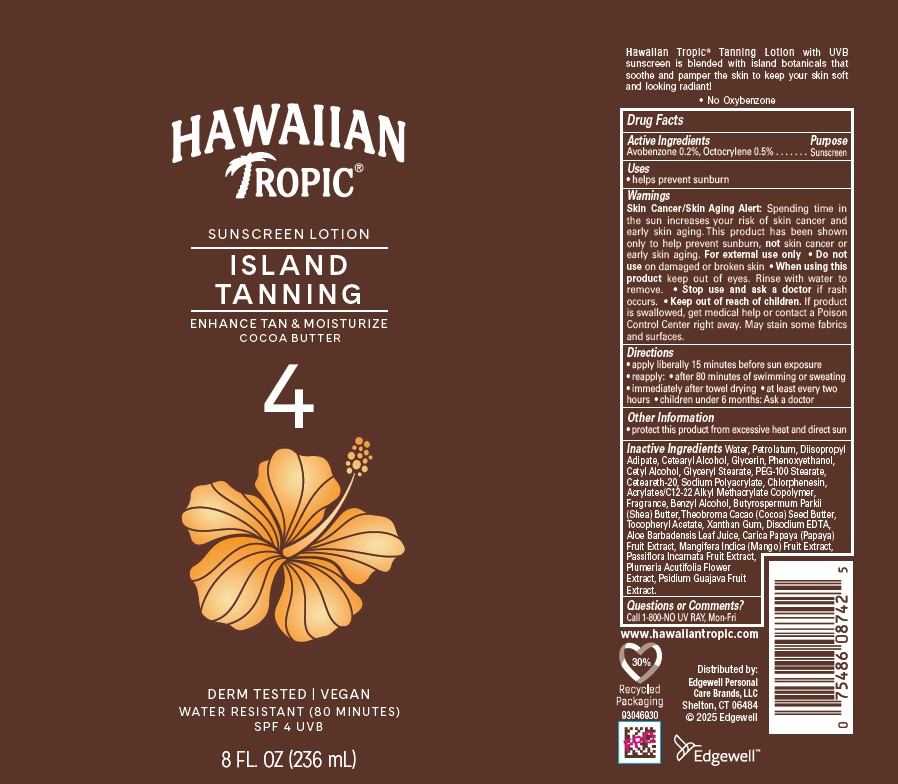 DRUG LABEL: HAWAIIAN TROPIC
NDC: 63354-972 | Form: LOTION
Manufacturer: Edgewell Personal Care Brands LLC
Category: otc | Type: HUMAN OTC DRUG LABEL
Date: 20250817

ACTIVE INGREDIENTS: AVOBENZONE 0.2 g/100 g; OCTOCRYLENE 0.5 g/100 g
INACTIVE INGREDIENTS: PHENOXYETHANOL; CARICA PAPAYA (PAPAYA) FRUIT; WATER; CETEARYL ALCOHOL; DIISOPROPYL ADIPATE; PEG-100 STEARATE; BENZYL ALCOHOL; ALOE BARBADENSIS LEAF; PSIDIUM GUAJAVA FRUIT; XANTHAN GUM; BUTYROSPERMUM PARKII (SHEA) BUTTER; CHLORPHENESIN; THEOBROMA CACAO (COCOA) SEED BUTTER; PLUMERIA RUBRA FLOWER; MANGIFERA INDICA (MANGO) FRUIT; ALPHA-TOCOPHEROL ACETATE; PASSIFLORA INCARNATA FRUIT; GLYCERYL STEARATE; GLYCERIN; CETEARETH-20; SODIUM POLYACRYLATE (2500000 MW); PETROLATUM; CETYL ALCOHOL; EDETATE DISODIUM

Active Ingredients

Avobenzone 0.2%, Octocrylene 0.5%

Purpose

Sunscreen

Uses

• helps prevent sunburn

Warnings

Skin Cancer/Skin Aging Alert: Spending time in the sun increases your risk of skin cancer and early skin aging. This product has been shown only to help prevent sunburn, not skin cancer or early skin aging.

For external use only

May stain some fabrics and surfaces.

Do not use

on damaged or broken skin

When using this product

keep out of eyes. Rinse with water to remove.

Stop use and ask a doctor

if rash occurs.

Keep out of reach of children.

If product is swallowed, get medical help or contact a Poison Control Center right away.

Directions

• apply liberally 15 minutes before sun exposure• reapply: • after 80 minutes of swimming or sweating • immediately after towel drying • at least every two hours • children under 6 months: Ask a doctor

Other Information

• protect this product from excessive heat and direct sun

Inactive Ingredients

Water, Petrolatum, Diisopropyl Adipate, Cetearyl Alcohol, Glycerin, Phenoxyethanol, Cetyl Alcohol, Glyceryl Stearate, PEG-100 Stearate, Ceteareth-20, Sodium Polyacrylate, Chlorphenesin, Acrylates/C12-22 Alkyl Methacrylate Copolymer, Fragrance, Benzyl Alcohol, Butyrospermum Parkii (Shea) Butter, Theobroma Cacao (Cocoa) Seed Butter, Tocopheryl Acetate, Xanthan Gum, Disodium EDTA, Aloe Barbadensis Leaf Juice, Carica Papaya (Papaya) Fruit Extract, Mangifera Indica (Mango) Fruit Extract, Passiflora Incarnata Fruit Extract, Plumeria Acutifolia Flower Extract, Psidium Guajava Fruit Extract.

Questions or Comments?

Call 1-800-NO UV RAY, Mon-Fri

Principal Display Panel

HAWAIIAN
TROPIC
SUNSCREEN LOTION
ISLAND
TANNING
ENHANCE TAN & MOISTURIZE
COCOA BUTTER
4
DERM TESTED | VEGAN
WATER RESISTANT (80 MINUTES)
SPF 4 UVB
8 FL. OZ (236 mL)